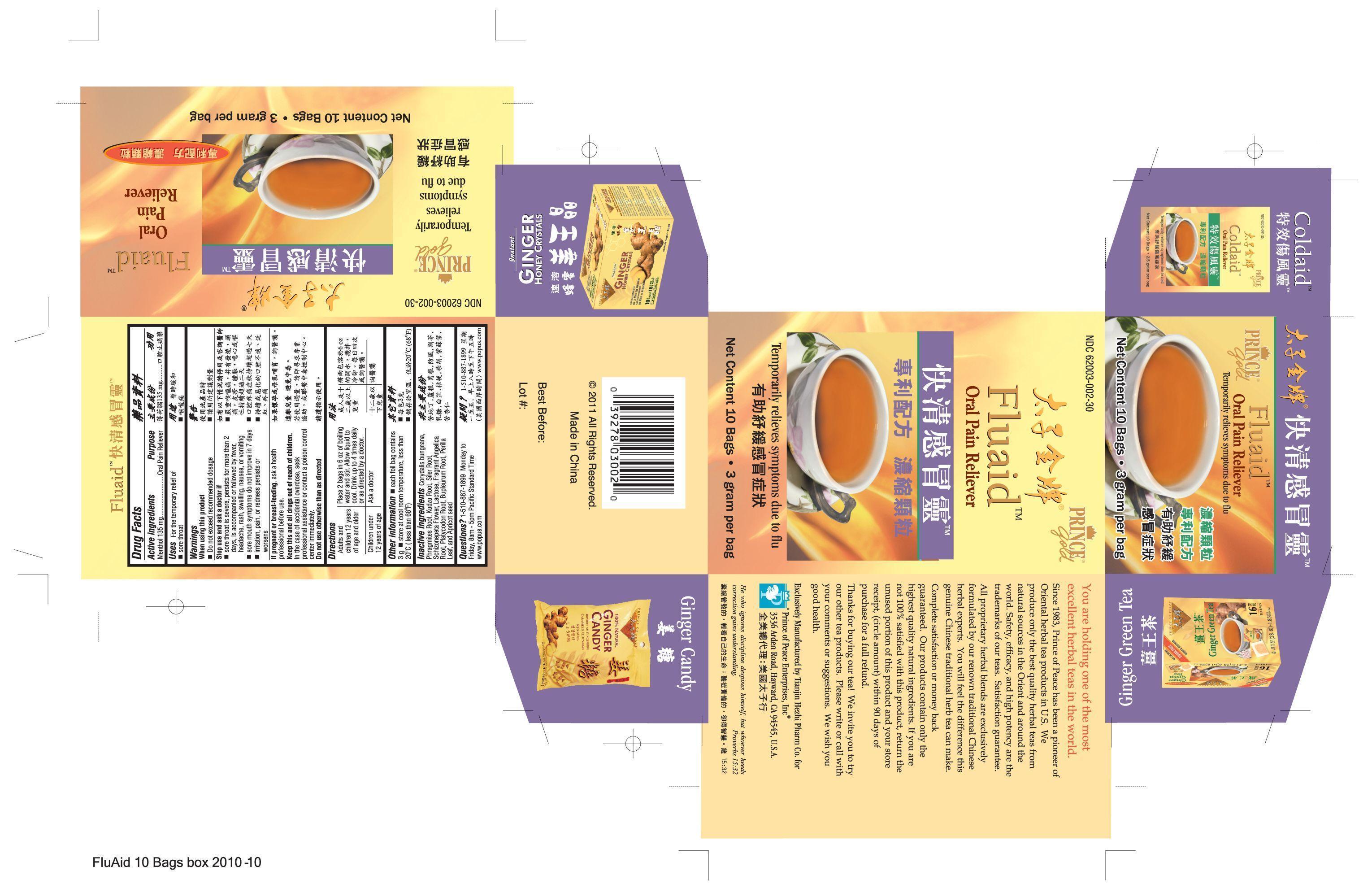 DRUG LABEL: Fluaid
NDC: 62003-002 | Form: GRANULE, FOR SOLUTION
Manufacturer: PRINCE OF PEACE ENTERPRISES INC.
Category: otc | Type: HUMAN OTC DRUG LABEL
Date: 20140401

ACTIVE INGREDIENTS: Menthol 270 mg/6 g
INACTIVE INGREDIENTS: Angelica dahurica root; Lactose; Bupleurum chinense root; APRICOT; PUERARIA MONTANA VAR. CHINENSIS ROOT; Saposhnikovia divaricata root; SCHIZONEPETA TENUFOLIA SPIKE; PLATYCODON GRANDIFLORUM LEAF; Perilla frutescens leaf; CORYDALIS BUNGEANA FLOWERING/FRUITING TOP ; PHRAGMITES AUSTRALIS ROOT

Drug Facts

Active ingredients Purpose

Menthol 135 mg.................Oral Pain Reliever

PURPOSE

Uses For the temporary relief of sore throat

When using this product

- Do not exceed recommended dosage

Stop use and ask a doctor if

- sore throat is severe, persists for more than 2 days, is accompanied or followed by fever, headache, rash, swelling, nausea, or vomiting
- sore mouth symptoms do not improve in 7 days
- irritation, pain, or redness persists or worsens

PREGNANCY OR BREAST FEEDING

If pregnant or breast-feeding, ask a health professional before use.

KEEP OUT OF REACH OF CHILDREN

Keep this and all drugs out of reach of children.

Do not use otherwise than as directed

WARNINGS

In the case of accidental overdose, seek professional assistance or contact a poison control center immediately.

QUESTIONS

- Questions? 1-510-887-1899 Monday to Friday, 8 am - 5 pm Pacific Standard Time

- www.popus.com

INDICATIONS AND USAGE

UsesFor the temporary relief of sore throat

Directions

Adults and children 12 years of age and older | Place 1 bags in 6 oz of boiling water and stir. Allow liquid to cool, Drink up to 4 times daily or as directed by a doctor
Children under 12 years of age | Ask A doctor

INACTIVE INGREDIENT

Corydalis bungeana, Phragmites Root, Kudzu Root, Siler Root, Schizonepeta Flower, Lactose, Fragrant Angelica Root, Platycodon Root, Bupleurum Root, Perilla Leaf, and Apricot Seed